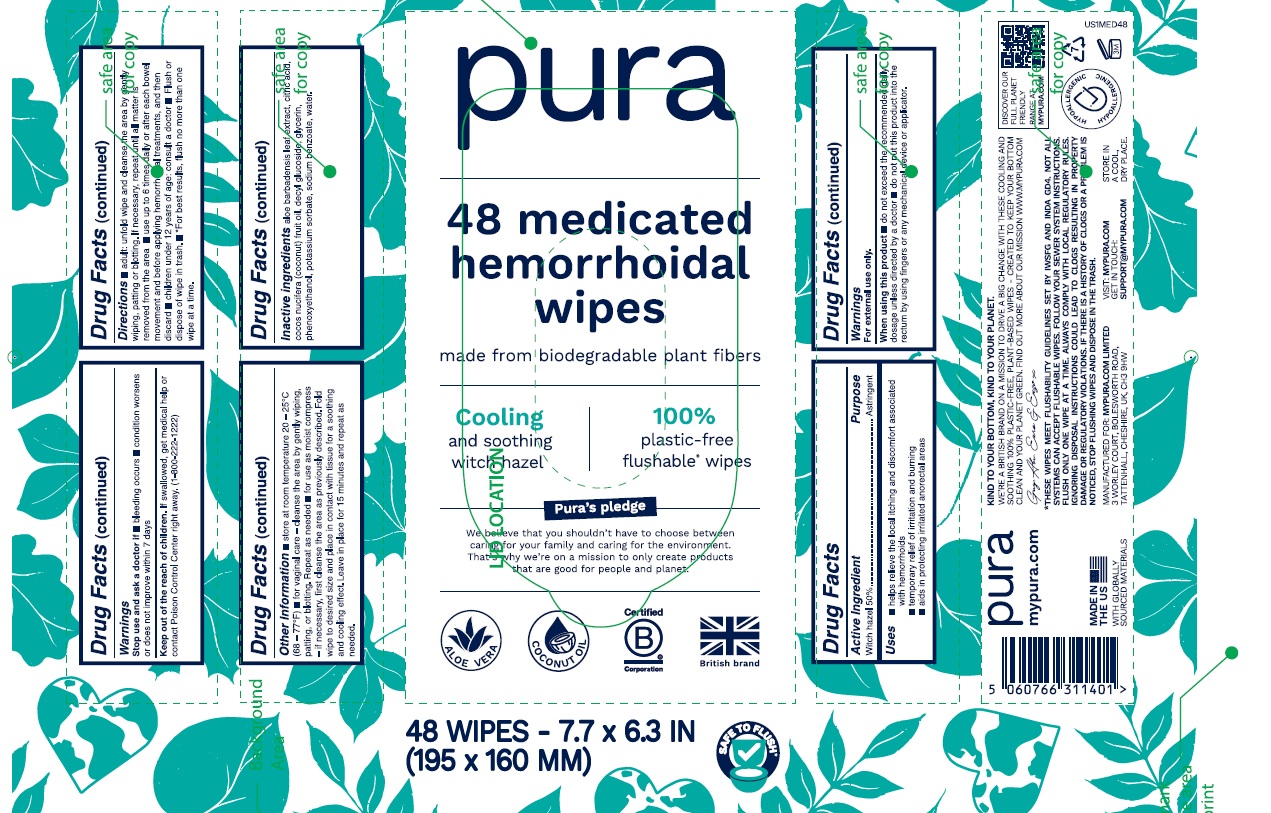 DRUG LABEL: PURA
NDC: 84217-050 | Form: CLOTH
Manufacturer: Mypura.com Limited
Category: otc | Type: HUMAN OTC DRUG LABEL
Date: 20251205

ACTIVE INGREDIENTS: WITCH HAZEL 50 mg/1 1
INACTIVE INGREDIENTS: ALOE VERA LEAF; ANHYDROUS CITRIC ACID; COCOS NUCIFERA WHOLE; DECYL GLUCOSIDE; GLYCERIN; PHENOXYETHANOL; SODIUM BENZOATE; WATER; POTASSIUM SORBATE

Active Ingredient

Witch Hazel 50%

Purpose

Astringent

Uses

- helps relieve the local itching and discomfort associated with hemmorhoids
- temporary relief of irritation and burning
- aids in protecting irritated anorectal areas

Warnings

For external use only

When using this product

- do not exceed the recommended daily dosage unless directed by a doctor
- do not put this product into the rectum by using fingers or any mechanical device or applicator

Stop use and ask a doctor if

- bleeding occurs
- condition worsens or does not improve within 7 days

Keep out of the reach of children

If swallowed, get medical help or contact Poison Control Center right away (1-800-222-1222)

Directions

- adult: unfold wipe and cleanse the area by gently wiping, patting or blotting. If necessary, repeat until all matter is removed from the area.
- use upto 6 times daily or after each bowel movement and before applying hemmorhoidal treatments and then discard.
- children under 12 years of age consult a doctor
- Flush or dispose of wipe in thrash
- For best results flush no more than one wipe at a time

Inactive Ingredients

aloe barbadensis leaf extract, citric acid, cocos nucifera (coconut) fruit oil, decyl glucoside, glycerin, phenoxythanol, potassium sorbate, sodium benzoate, water.

Other Information

- store at room temperature 20 - 25 ºC (68 - 77ºF)
- for vaginal care- cleanse the area by gently wiping, patting or blotting. Repeat as needed
- for use as moist compress - if necessary, first cleanse the area as previously described. Fold wipe to desired size and place in contact with tissue for a soothing and cooling effect. Leave in place for 15 minutesand repeat as needed.

Principal Display Panel

Pura

48 medicated hemmorhoidal wipes

made from biodegradable plant fibers

Cooling and soothing Witch hazel

100% plastic-free flushable wipes

Pura's Pledge

We believe that you shouldn't have to choose between caring for your famile and caring for the environment. That's why we are on a mission to only create products that are good for people and planets.

48 WIPES - 7.7 X 6.3 IN

(195 X 160 MM)